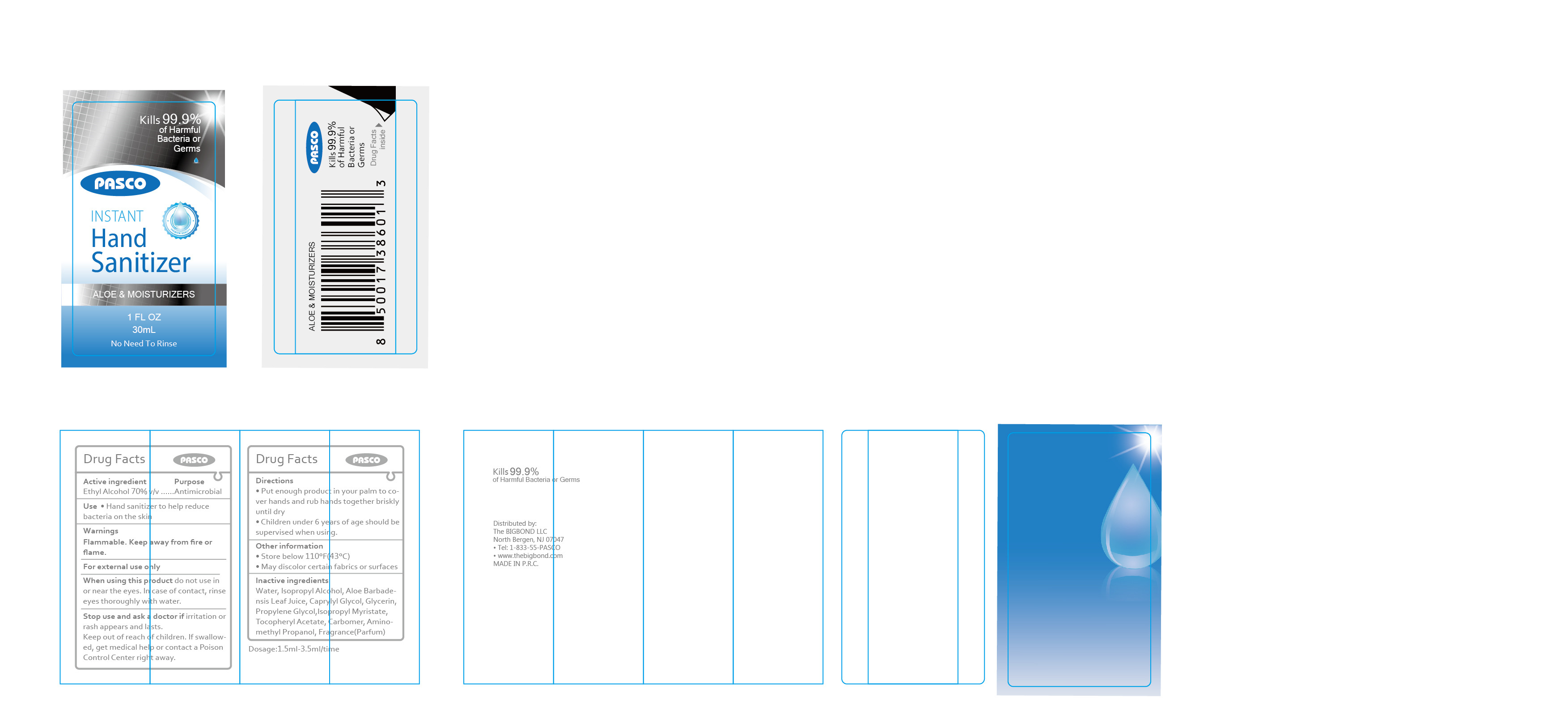 DRUG LABEL: Instant hand sanitizer
NDC: 52903-002 | Form: LIQUID
Manufacturer: Ningbo Pasco United Industry Co.,Ltd.
Category: otc | Type: HUMAN OTC DRUG LABEL
Date: 20210203

ACTIVE INGREDIENTS: ALCOHOL 21 mL/30 mL
INACTIVE INGREDIENTS: ALOE VERA LEAF; AMINOMETHYLPROPANOL; WATER; ISOPROPYL ALCOHOL; .ALPHA.-TOCOPHEROL ACETATE; CARBOMER HOMOPOLYMER, UNSPECIFIED TYPE; CAPRYLYL GLYCOL; GLYCERIN; PROPYLENE GLYCOL; ISOPROPYL MYRISTATE

DOSAGE AND ADMINISTRATION

1.5ml-3.5ml/time；Store below 110℉（43℃）；May discolor certain fabrics of surfaces

WARNINGS

keep out of reach of childen

INACTIVE INGREDIENT

Water, Isopropyl Alcohol, Aloe Barbadensis Leaf Juice, Caprylyl Glycol, Glycerin, Propylene Glycol ,Isopropyl Myristate, Tocopheryl Acetate, Carbomer, Aminomethyl Propanol

INDICATIONS AND USAGE

Take appropriate amount of this product to moisten your hands and rub for one minute until the liquid covers the whole surface

keep out of reach of children

PURPOSE

Disinfection
Sterilization
No Rinseing

ACTIVE INGREDIENT

Ethyl alcoho